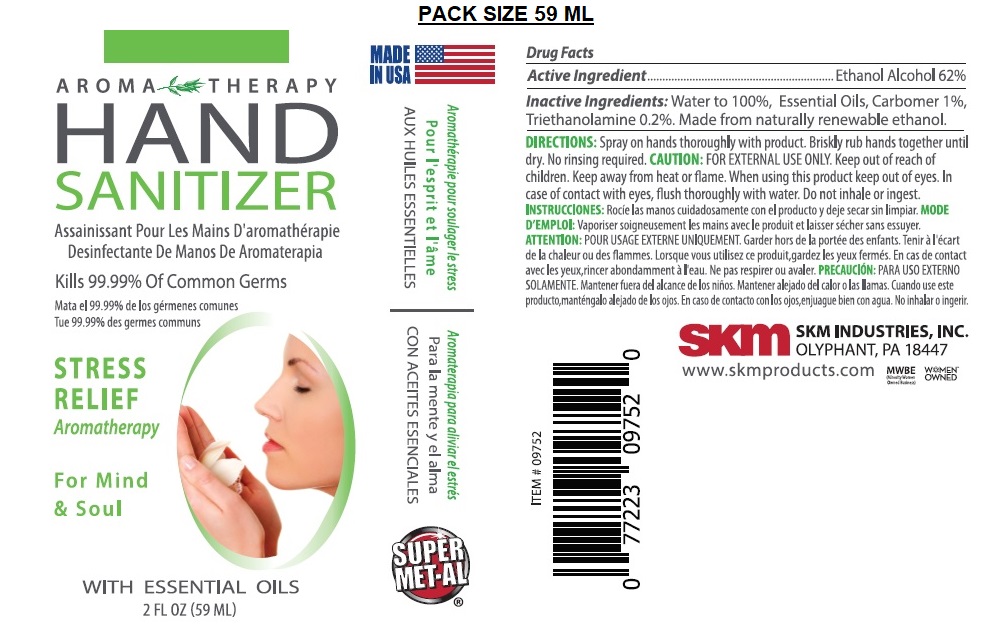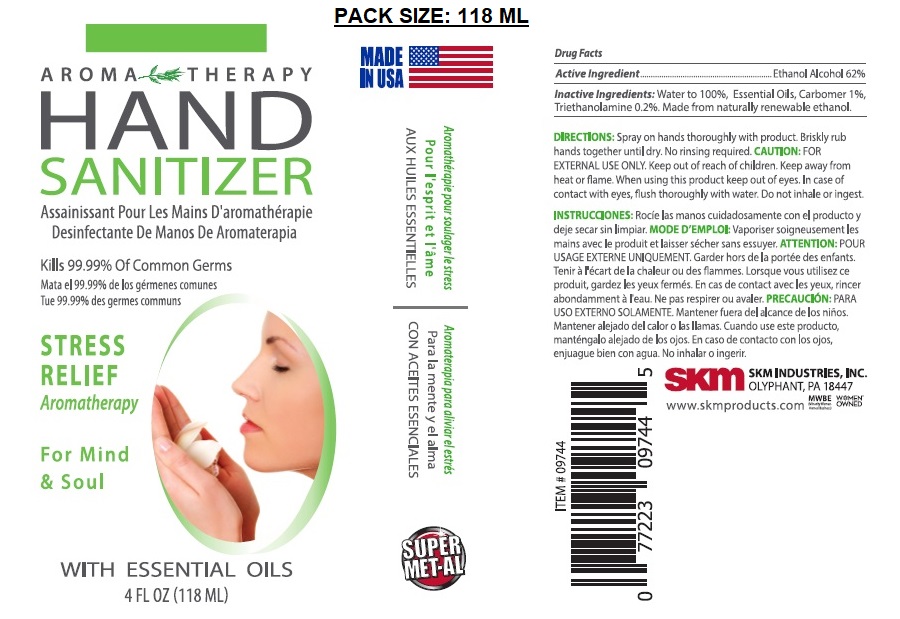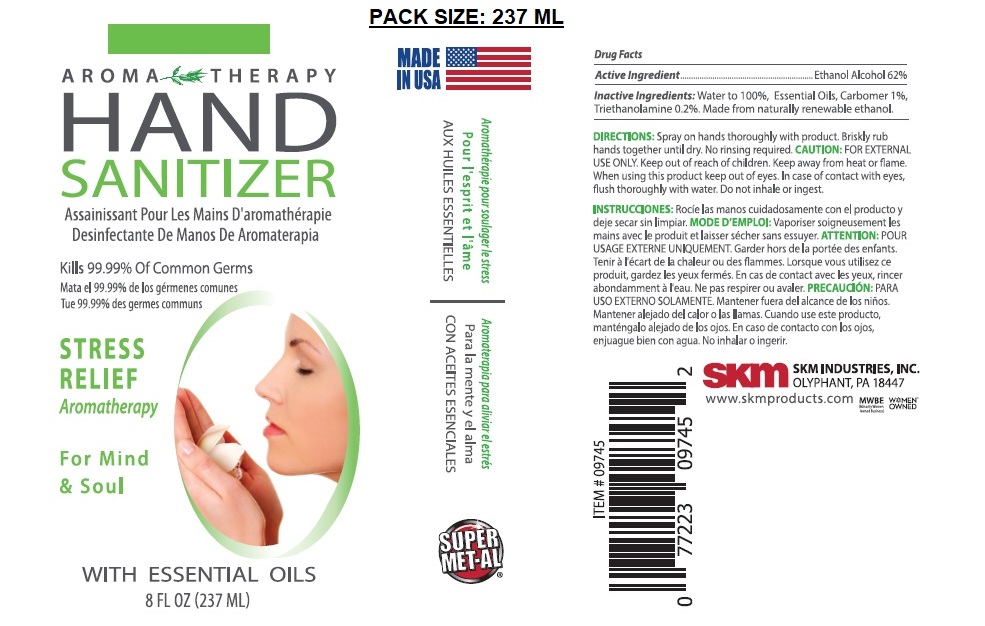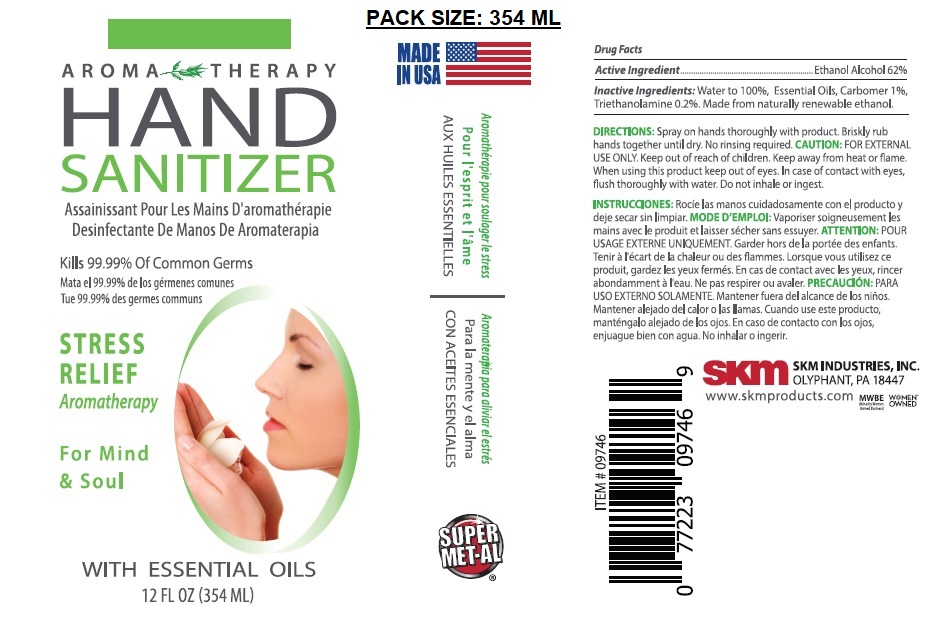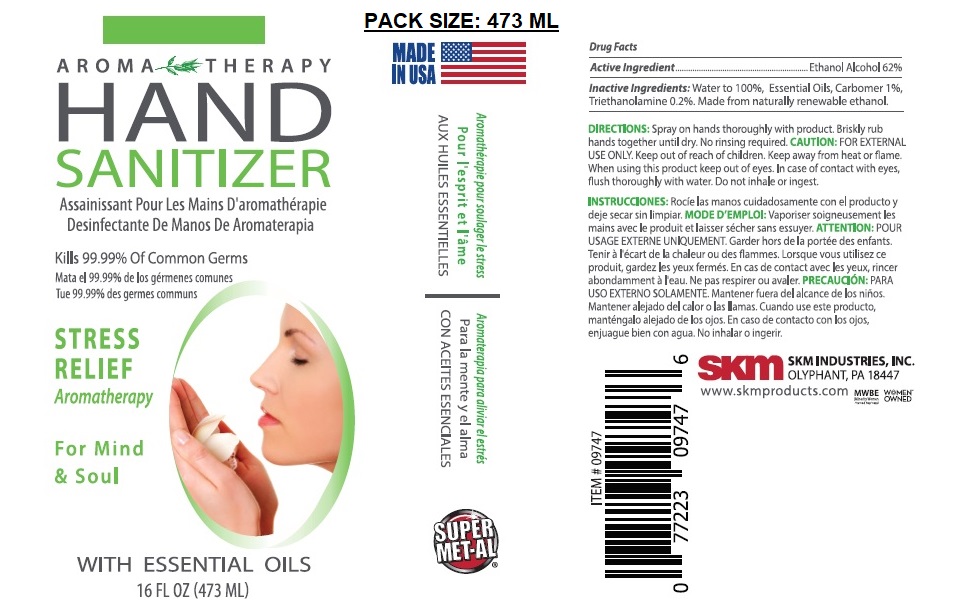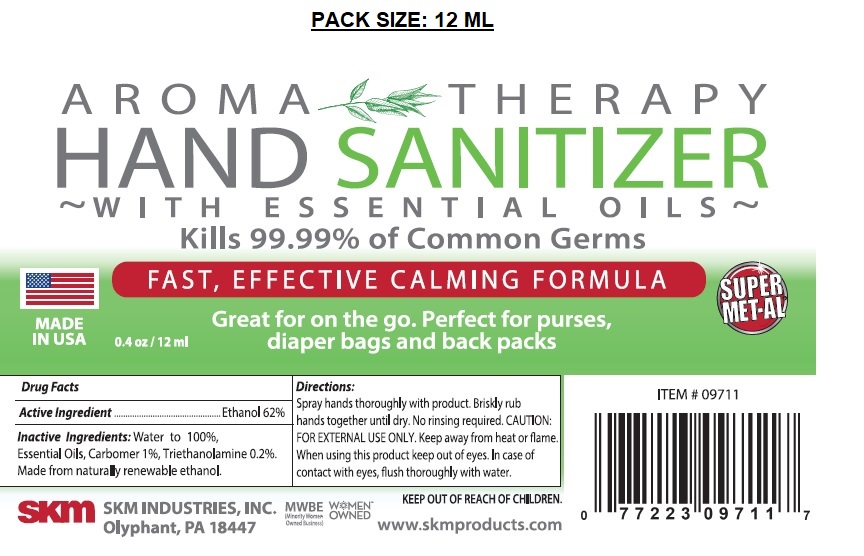 DRUG LABEL: Super Met-Al Aromatherapy Hand Sanitizer
NDC: 74990-001 | Form: SPRAY
Manufacturer: Skm Industries Inc.
Category: otc | Type: HUMAN OTC DRUG LABEL
Date: 20200714

ACTIVE INGREDIENTS: ALCOHOL 62 mL/100 mL
INACTIVE INGREDIENTS: WATER; CARBOMER HOMOPOLYMER, UNSPECIFIED TYPE; TROLAMINE

AROMA THERAPY HAND SANITIZER

Active Ingredient

Ethanol Alcohol 62%

Purpose

Antiseptic

Use

Hand Sanitizer to help reduce bacteria that potentially can cause disease.

WARNINGS

CAUTION: FOR EXTERNAL USE ONLY.

Keep away from heat or flame.

When using this product keep out of eyes. In case of contact with eyes, flush thoroughly with water. Do not inhale or ingest.

Keep out of reach of children.

DOSAGE AND ADMINISTRATION

DIRECTIONS: Spray on hands thoroughly with product. Briskly rub hands together until dry. No rinsing required.

INACTIVE INGREDIENT

Inactive Ingredients: Water to 100%, Essential Oils, Carbomer 1%, Triethanolamine 0.2%. Made from naturally renewable ethanol.

MADE IN USA

Kills 99.99% of Common Germs

STRESS RELIEF

Aromatherapy

For Mind & Soul

WITH ESSENTIAL OILS

FAST, EFFECTIVE CALMING FORMULA

Great for on the go. Perfect for purses, diaper bags and back packs

SUPER-MET-AL

SKM INDUSTRIES, INC.

OLYPHANT, PA 18447

MWBE (Minority Women Owned Business)

WOMEN OWNED™

www.skmproducts.com